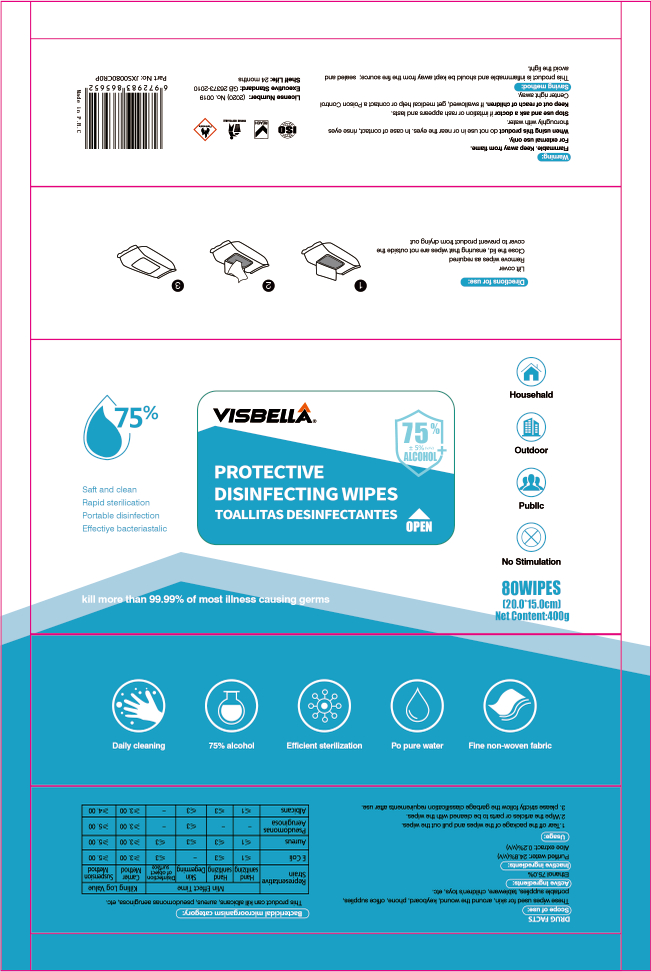 DRUG LABEL: disinfecting wipes
NDC: 40760-018 | Form: CLOTH
Manufacturer: Huzhou Guoneng New Material Co., Ltd.
Category: otc | Type: HUMAN OTC DRUG LABEL
Date: 20200716

ACTIVE INGREDIENTS: ALCOHOL 352.94 mL/80 1
INACTIVE INGREDIENTS: WATER; ALOE

DOSAGE AND ADMINISTRATION

This product is inflammable and should be kept away from the fire source; sealed and avoid the light.

INACTIVE INGREDIENT

Purified water, aloe extract

INDICATIONS AND USAGE

1.Tear off the package of the wipes and pull out the wipes.
2.Wipe the articles or parts to be cleaned with the wipes.
3. please stricty fllowo the garbage classification requirements after use.

ACTIVE INGREDIENT

Ethanol

keep out of reach of children

PURPOSE

Disinfection
Sterilization
No Rinseing

WARNINGS

Flammable. Keep away from fiame.For external use only.